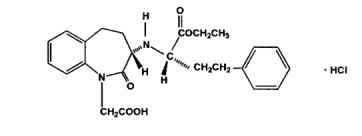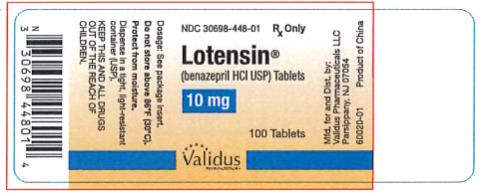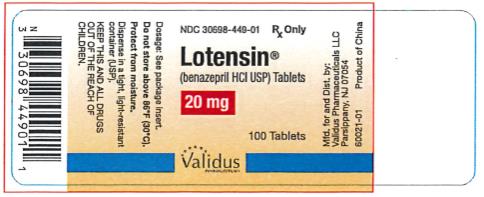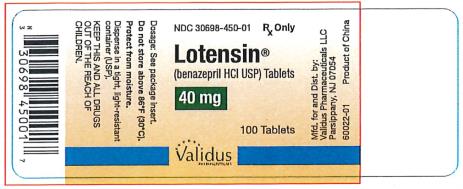 DRUG LABEL: Lotensin
NDC: 30698-449 | Form: TABLET
Manufacturer: Validus Pharmaceuticals LLC
Category: prescription | Type: HUMAN PRESCRIPTION DRUG LABEL
Date: 20250930

ACTIVE INGREDIENTS: BENAZEPRIL HYDROCHLORIDE 20 mg/1 1
INACTIVE INGREDIENTS: SILICON DIOXIDE; CROSPOVIDONE; HYDROGENATED CASTOR OIL; HYPROMELLOSES; FERRIC OXIDE RED; LACTOSE, UNSPECIFIED FORM; CELLULOSE, MICROCRYSTALLINE; POLYSORBATE 80; STARCH, CORN; TALC; TITANIUM DIOXIDE

HIGHLIGHTS OF PRESCRIBING INFORMATION

These highlights do not include all the information needed to use LOTENSIN® safely and effectively. See full prescribing information for use LOTENSIN®.
LOTENSIN® (benazepril hydrochloride, USP) tablets, for oral use
Initial U.S. Approval: 1991

WARNING-FETAL TOXICITY

See full prescribinginformation forcomplete boxed warning.

When pregnancyis detected, discontinue Lotensin as soon as possible.(5.1)

Drugs that act directly on the renin-angiotensin system can cause injury and death to the developing fetus. (5.1)

1. INDICATIONS AND USAGE

Lotensin is an angiotensin-converting enzyme (ACE) inhibitor indicated for the treatment of hypertension, to lower blood pressure. Lowering blood pressure reduces the risk of fatal and nonfatal cardiovascular events, primarily strokes and myocardial infarctions. (1)

2. DOSAGE AND ADMINISTRATION

- Adult Patients: Initiate with 10 mg once daily (or 5 mg if patients is on diuretic). Titrate to 40 mg daily based on blood pressure response. (2.1)
- Pediatric patients age 6 years and above with glomerular filtration rate (GFR) >30 mL/min/1.73 m^2: Initiate with 0.2 mg/kg once daily. Maximum dose is 0.6 mg/kg once daily.
- Renal Impairment: Initiate with 5 mg once daily in patients with GFR <30 mL/min/1.73 m^2(serum creatinine >3 mg/dL) (2.2)

3. DOSAGE FORMS AND STRENGTHS

- Tablets: 10 mg, 20 mg, 40 mg

4. CONTRAINDICATIONS

- Angioedema or history of hereditary or idiopathic angioedema (4)
- Hypersensitivity (4)
- Coadministration with aliskiren in patients with diabetes (4)

5. WARNINGS AND PRECAUTIONS

- Angioedema: Discontinue Lotensin and treat appropriately. (5.2)
- Monitor renal function periodically. (5.3)
- Monitor blood pressure after initiation. (5.4)
- Hyperkalemia: Monitor serum potassium periodically. (5.5)
- Hepatic toxicity: Monitor for jaundice or signs of liver failure. (5.6)

6. ADVERSE REACTIONS

The most common adverse reactions leading to discontinuation were headache (0.6%) and cough (0.5%) (6)

To report SUSPECTED ADVERSE REACTIONS, contact Validus Pharmaceuticals LLC at 1-866-982-5438 (1-866-9VALIDUS) or FDA at 1-800-FDA-1088 or www.fda.gov/medwatch.

7. DRUG INTERACTIONS

- Diuretics: Excessive drop in blood pressure (7.1)
- Antidiabetics: Increased risk of hypoglycemia (7.2)
- NSAIDS: Increased risk of renal impairment and loss of antihypertensive efficacy (7.3)
- Dual inhibition of the renin-angiotensin system: Increased risk of renal impairment, hypotension and hyperkalemia (7.4)
- Lithium: Symptoms of lithium toxicity (7.6)
- Neprilysin Inhibitor: Increased risk of angioedema (7.7)
- Gold: Nitritoid reactions (7.8)

8. USE IN SPECIFIC POPULATIONS

- Pediatrics: Safety and effectiveness have not been established in patients < 6 years of age or with GFR < 30 mL/min/1.73m^2(8.3)
- Race: Less antihypertensive effect in Blacks as monotherapy (8.5)

FULL PRESCRIBING INFORMATION

WARNING: FETAL TOXICITY

When pregnancy is detected, discontinueLotensin as soon as possible.

Drugs thatactdirectlyon the renin-angiotensin system can causeinjury and death to the developing fetus [see Warnings and Precautions (5.1)].

1. INDICATIONS AND USAGE

Lotensin®is indicated for the treatment of hypertension, to lower blood pressure. Lowering blood pressure reduces the risk of fatal and nonfatal cardiovascular events, primarily strokes and myocardial infarctions. These benefits have been seen in controlled trials of antihypertensive drugs from a wide variety of pharmacologic classes including the class to which this drug principally belongs.

Control of high blood pressure should be part of comprehensive cardiovascular risk management, including, as appropriate, lipid control, diabetes management, antithrombotic therapy, smoking cessation, exercise, and limited sodium intake. Many patients will require more than one drug to achieve blood pressure goals. For specific advice on goals and management, see published guidelines, such as those of the National High Blood Pressure Education Program’s Joint National Committee on Prevention, Detection, Evaluation, and Treatment of High Blood Pressure (JNC).

Numerous antihypertensive drugs, from a variety of pharmacologic classes and with different mechanisms of action, have been shown in randomized controlled trials to reduce cardiovascular morbidity and mortality, and it can be concluded that it is blood pressure reduction, and not some other pharmacologic property of the drugs, that is largely responsible for those benefits. The largest and most consistent cardiovascular outcome benefit has been a reduction in the risk of stroke, but reductions in myocardial infarction and cardiovascular mortality also have been seen regularly.

Elevated systolic or diastolic pressure causes increased cardiovascular risk, and the absolute risk increase per mm Hg is greater at higher blood pressures, so that even modest reductions of severe hypertension can provide substantial benefit. Relative risk reduction from blood pressure reduction is similar across populations with varying absolute risk, so the absolute benefit is greater in patients who are at higher risk independent of their hypertension (for example, patients with diabetes or hyperlipidemia), and such patients would be expected to benefit from more aggressive treatment to a lower blood pressure goal.

Some antihypertensive drugs have smaller blood pressure effects (as monotherapy) in Black patients, and many antihypertensive drugs have additional approved indications and effects (e.g., on angina, heart failure, or diabetic kidney disease). These considerations may guide selection of therapy.

It may be used alone or in combination with thiazide diuretics.

2. DOSAGE AND ADMINISTRATION

2.1 Recommended Dosage

ADULTS

The recommended initial dose for patients not receiving a diuretic is 10 mg once a day. The usual maintenance dosage range is 20 to 40 mg per day administered as a single dose or in two equally divided doses. A dose of 80 mg gives an increased response, but experience with this dose is limited. The divided regimen was more effective in controlling trough (pre-dosing) blood pressure than the same dose given as a once-daily regimen.

Use with diuretics inadults

The recommended starting dose of Lotensin in a patient on a diuretic is 5 mg once daily. If blood pressure is not controlled with Lotensin alone, a low dose of diuretic may be added.

PEDIATRIC PATIENTS 6 YEARS OF AGE ANDOLDER

The recommended starting dose for pediatric patients is 0.2 mg/kg once per day. Titrate as needed to 0.6 mg/kg once per day. Doses above 0.6 mg/kg (or in excess of 40 mg daily) have not been studied in pediatric patients.

Lotensin is not recommended in pediatric patients less than 6 years of age or in pediatric patients with GFR less than 30 mL/min/1.73m² [see Use in Specific Populations (8.3)].

2.2 Dose Adjustment for Renal Impairment

For adults with a GFR <30 mL/min/1.73 m²(serum creatinine >3 mg/dL), the recommended initial dose is 5 mg Lotensin once daily. Dosage may be titrated upward until blood pressure is controlled or to a maximum total daily dose of 40 mg. Lotensin can also worsen renal function [see Warnings and Precautions (5.3)].

2.3 Preparation of Suspension (for 150 mL of a 2 mg/mL Suspension)

Add 75 mL of Ora-Plus®* oral suspending vehicle to an amber polyethylene terephthalate (PET) bottle containing fifteen Lotensin 20 mg tablets, and shake for at least two minutes. Allow the suspension to stand for a minimum of 1 hour. After the standing time, shake the suspension for a minimum of one additional minute. Add 75 mL of Ora-Sweet®* oral syrup vehicle to the bottle and shake the suspension to disperse the ingredients. The suspension should be refrigerated at 2º to 8°C (36º to 46°F) and can be stored for up to 30 days in the PET bottle with a child-resistant screw- cap closure. Shake the suspension before each use.

*Ora-Plus® and Ora-Sweet® are registered trademarks of Paddock Laboratories, Inc. Ora Plus® contains carrageenan, citric acid, methylparaben, microcrystalline cellulose, carboxymethylcellulose sodium, potassium sorbate, simethicone, sodium phosphate monobasic, xanthan gum, and water. Ora-Sweet® contains citric acid, berry citrus flavorant, glycerin, methylparaben, potassium sorbate, sodium phosphate monobasic, sorbitol, sucrose, and water.

3. DOSAGE FORMS AND STRENGTHS

Tablets: 10 mg, 20 mg, and 40 mg

- Each 10 mg tablet is dark yellow with “10” on one side and “LOTENSIN” on the other
- Each 20 mg tablet is pink with “20” on one side and “LOTENSIN” on the other
- Each 40 mg tablet is dark rose with “40” on one side and “LOTENSIN” on the other

4. CONTRAINDICATIONS

Lotensin is contraindicated in patients:

- who are hypersensitive to benazepril or to any other ACE inhibitor
- with a history of angioedema with or without previous ACE inhibitor treatment

Lotensin is contraindicated in combination with a neprilysin inhibitor (e.g., sacubitril). Do not administer Lotensin within 36 hours of switching to or from sacubitril/valsartan, a neprilysin inhibitor [see Warnings and Precautions (5.2)].

Do not coadminister aliskiren with angiotensin receptor blockers, ACE inhibitors, including Lotensin in patients with diabetes [see Drug Interactions (7.4)].

5. WARNINGS AND PRECAUTIONS

5.1 Fetal Toxicity

Lotensin can cause fetal harm when administered to a pregnant woman. Use of drugs that act on the renin-angiotensin system during the second and third trimesters of pregnancy reduces fetal renal function and increases fetal and neonatal morbidity and death.

Resulting oligohydramnios can be associated with fetal lung hypoplasia and skeletal deformations. Potential neonatal adverse effects include skull hypoplasia, anuria, hypotension, renal failure, and death. When pregnancy is detected, discontinue Lotensin as soon as possible [see Use in Specific Populations (8.1)].

5.2 Angioedema and Anaphylactoid Reactions

Angioedema

Head and Neck Angioedema

Angioedema of the face, extremities, lips, tongue, glottis, and/or larynx including some fatal reactions, have occured in patients treated with Lotensin. Patients with involvement of the tongue, glottis or larynx are likely to experience airway obstruction, especially those with a history of airway surgery. Lotensin should be promptly discontinued and appropriate therapy and monitoring should be provided until complete and sustained resolution of signs and symptoms of angioedema has occurred.

Patients with a history of angioedema unrelated to ACE inhibitor therapy may be at increased risk of angioedema while receiving an ACE inhibitor [see Contraindications (4)]. ACE inhibitors have been associated with a higher rate of angioedema in Black than in non-Black patients.

Patients receiving coadministration of ACE inhibitor and mTOR (mammalian target of rapamycin) inhibitor (e.g., temsirolimus, sirolimus, everolimus) therapy or a neprilysin inhibitor may be at increased risk for angioedema [see Drug Interactions (7.7)].

Intestinal Angioedema

Intestinal angioedema has occurred in patients treated with ACE inhibitors. These patients presented with abdominal pain (with or without nausea or vomiting); in some cases there was no prior history of facial angioedema and C-1 esterase levels were normal. In some cases, the angioedema was diagnosed by procedures including abdominal CT scan or ultrasound, or at surgery, and symptoms resolved after stopping the ACE inhibitor.

Anaphylactoid Reactions

Anaphylactoid Reactions During Desensitization

Two patients undergoing desensitizing treatment with hymenoptera venom while receiving ACE inhibitors sustained life-threatening anaphylactoid reactions.

Anaphylactoid Reactions During Dialysis

Sudden and potentially life threatening anaphylactoid reactions have occurred in some patients dialyzed with high-flux membranes and treated concomitantly with an ACE inhibitor. In such patients, dialysis must be stopped immediately, and aggressive therapy for anaphylactoid reactions must be initiated. Symptoms have not been relieved by antihistamines in these situations. In these patients, consideration should be given to using a different type of dialysis membrane or a different class of antihypertensive agent. Anaphylactoid reactions have also been reported in patients undergoing low-density lipoprotein apheresis with dextran sulfate absorption.

5.3 Impaired Renal Function

Monitor renal function periodically in patients treated with Lotensin. Changes in renal function, including acute renal failure, can be caused by drugs that inhibit the renin-angiotensin system.

Patients whose renal function may depend on the activity of the renin-angiotensin system (e.g., patients with renal artery stenosis, chronic kidney disease, severe congestive heart failure, post- myocardial infarction, or volume depletion) may be at particular risk of developing acute renal failure on Lotensin. Consider withholding or discontinuing therapy in patients who develop a clinically significant decrease in renal function on Lotensin.

5.4 Hypotension

Lotensin can cause symptomatic hypotension, sometimes complicated by oliguria, progressive azotemia, acute renal failure, or death. Patients at risk of excessive hypotension include those with the following conditions or characteristics: heart failure with systolic blood pressure below 100 mm Hg, ischemic heart disease, cerebrovascular disease, hyponatremia, high dose diuretic therapy, renal dialysis, or severe volume and/or salt depletion of any etiology.

In such patients, follow closely for the first 2 weeks of treatment and whenever the dose of benazepril or diuretic is increased. Avoid use of Lotensin in patients who are hemodynamically unstable after acute MI.

Surgery/Anesthesia

In patients undergoing major surgery or during anesthesia with agents that produce hypotension, Lotensin may block angiotensin II formation secondary to compensatory renin release. If hypotension occurs, correct by volume expansion.

5.5 Hyperkalemia

Serum potassium should be monitored periodically in patients receiving Lotensin. Drugs that inhibit the renin-angiotensin system can cause hyperkalemia. Risk factors for the development of hyperkalemia include renal insufficiency, diabetes mellitus, and the concomitant use of potassium-sparing diuretics, potassium supplements and/or potassium-containing salt substitutes [see Drug Interactions (7.1)].

5.6 Hepatic Failure

ACE inhibitors have been associated with a syndrome that starts with cholestatic jaundice and progresses to fulminant hepatic necrosis and (sometimes) death. The mechanism of this syndrome is not understood. Patients receiving ACE inhibitors who develop jaundice or marked elevations of hepatic enzymes should discontinue the ACE inhibitor and receive appropriate medical follow-up.

6. ADVERSE REACTIONS

Because clinical trials are conducted under widely varying conditions, adverse reaction rates observed in the clinical studies of a drug cannot be directly compared to rates in the clinical studies of another drug and may not reflect the rates observed in practice.

Lotensin has been evaluated for safety in over 6000 patients with hypertension; over 700 of these patients were treated for at least one year. The overall incidence of reported adverse events was similar in Lotensin and placebo patients.

The reported side effects were generally mild and transient, and there was no relation between side effects and age, duration of therapy, or total dosage within the range of 2 to 80 mg.

Discontinuation of therapy because of a side effect was required in approximately 5% of U.S. patients treated with Lotensin and in 3% of patients treated with placebo. The most common reasons for discontinuation were headache (0.6%) and cough (0.5%).

Adverse reactions seen in at least 1% greater frequency in patients treated with Lotensin than placebo were headache (6% vs. 4%), dizziness (4% vs. 2%), somnolence (2% vs. 0%) and postural dizziness (2% vs. 0%).

Adverse reactions reported in controlled clinical trials (less than 1% more on benazepril than on placebo), and rarer events seen in post-marketing experience, include the following (in some, a causal relationship to drug use is uncertain):

Dermatologic: Stevens-Johnson syndrome, pemphigus, apparent hypersensitivity reactions (manifested by dermatitis, pruritus, or rash), photosensitivity, and flushing.

Gastrointestinal: Nausea, pancreatitis, constipation, gastritis, vomiting, and melena.

Hematologic: Thrombocytopenia and hemolytic anemia.

Neurologic/Psychiatric: Anxiety, decreased libido, hypertonia, insomnia, nervousness, and paresthesia.

Other: Fatigue, asthma, bronchitis, dyspnea, sinusitis, urinary tract infection, frequent urination, infection, arthritis, impotence, alopecia, arthralgia, myalgia, asthenia, sweating.

Laboratory Abnormalities:

Elevations of uric acid, blood glucose, serum bilirubin, and liver enzymes [see Warnings and Precautions (5)]have been reported, as have incidents of hyponatremia, electrocardiographic changes, eosinophilia, and proteinuria.

7. DRUG INTERACTIONS

7.1 Diuretics

Hypotension

Patients on diuretics, especially those in whom diuretic therapy was recently instituted, may occasionally experience an excessive reduction of blood pressure after initiation of therapy with Lotensin. The possibility of hypotensive effects with Lotensin can be minimized by either discontinuing or decreasing the dose of diuretic prior to initiation of treatment with Lotensin [see Dosage and Administration (2.1)].

Hyperkalemia

Potassium-sparing diuretics (spironolactone, amiloride, triamterene, and others) can increase the risk of hyperkalemia. Therefore, if concomitant use of such agents is indicated, monitor the patient’s serum potassium frequently. Lotensin attenuates potassium loss caused by thiazide-type diuretics.

7.2 Antidiabetics

Concomitant administration of Lotensin and antidiabetic medicines (insulins, oral hypoglycemic agents) may increase the risk of hypoglycemia.

7.3 Non-Steroidal Anti-Inflammatory Agents including Selective Cyclooxygenase-2 Inhibitors (COX-2 Inhibitors)

In patients who are elderly, volume-depleted (including those on diuretic therapy), or with compromised renal function, coadministration of NSAIDs, including selective COX-2 inhibitors, with ACE inhibitors, including benazepril, may result in deterioration of renal function, including possible acute renal failure. These effects are usually reversible. Monitor renal function periodically in patients receiving benazepril and NSAID therapy.

The antihypertensive effect of ACE inhibitors, including benazepril, may be attenuated by NSAIDs.

7.4 Dual Blockade of the Renin-Angiotensin System (RAS)

Dual Blockade of the RAS with angiotensin receptor blockers, ACE inhibitors, or aliskiren is associated with increased risks of hypotension, hyperkalemia, and changes in renal function (including acute renal failure) compared to monotherapy. Most patients receiving the combination of two RAS inhibitors do not obtain any additional benefit compared to monotherapy. In general, avoid combined use of RAS inhibitors. Closely monitor blood pressure, renal function and electrolytes in patients on Lotensin and other agents that affect the RAS.

Do not coadminister aliskiren with Lotensin in patients with diabetes. Avoid use of aliskiren with Lotensin in patients with renal impairment (GFR < 60 mL/min).

7.5 Mammalian Target of Rapamycin (mTOR) Inhibitors

Patients receiving coadministration of ACE inhibitor and mTOR inhibitor (e.g., temsirolimus, sirolimus, everolimus) therapy may be at increased risk for angioedema. Monitor for signs of angioedema [see Warnings and Precautions (5.2)].

7.6 Lithium

Lithium toxicity has been reported in patients receiving lithium concomitantly with Lotensin. Lithium toxicity was usually reversible upon discontinuation of lithium or Lotensin. Monitor serum lithium levels during concurrent use.

7.7 Neprilysin Inhibitor

Patients taking concomitant neprilysin inhibitors may be at increased risk for angioedema [see Warnings and Precautions].

7.8 Gold

Nitritoid reactions (symptoms include facial flushing, nausea, vomiting and hypotension) have been reported rarely in patients on therapy with injectable gold (sodium aurothiomalate) and concomitant ACE inhibitor therapy.

8. USE IN SPECIFIC POPULATIONS

8.1 Pregnancy

Risk Summary

Lotensin can cause fetal harm when administered to a pregnant woman. Use of drugs that act on the renin-angiotensin system during the second and third trimesters of pregnancy reduces fetal renal function and increases fetal and neonatal morbidity and death. Most epidemiologic studies examining fetal abnormalities after exposure to antihypertensive use in the first trimester have not distinguished drugs affecting the renin angiotensin system from other antihypertensive agents. When pregnancy is detected, discontinue Lotensin as soon as possible.

The estimated background risk of major birth defects and miscarriage for the indicated population are unknown. All pregnancies have a background risk of birth defects, loss, or other adverse outcomes. In the general U.S. population, the estimated background risk of major defects and miscarriage in clinically recognized pregnancies is 2-4% and 15-20%, respectively.

Clinical Considerations

Disease-associated maternal and/or embryo/fetal risk

Hypertension in pregnancy increases the maternal rush for pre-eclampsia, gestational diabetes, premature delivery, and delivery complications (e.g., need for cesarean section, and post-partum hemorrhage). Hypertension increases the fetal risk for intrauterine growth restriction and intrauterine death. Pregnant women with hypertension should be carefully monitored and managed accordingly.

Fetal/Neonatal Adverse Reactions

Oligohydramnios in pregnant women who use drugs affecting the renin-angiotensin system in the second and third trimesters of pregnancy can result in the following: reduced fetal renal function leading to anuria and renal failure, fetal lung hypoplasia and skeletal deformations, including skull hypoplasia, hypotension, and death. In the unusual case that there is no appropriate alternative to therapy with drugs affecting the renin-angiotensin system for a particular patient, apprise the mother of the potential risk to the fetus.

Perform serial ultrasound examinations to assess the intra-amniotic environment.

Fetal testing may be appropriate, based on the week of pregnancy. Patients and physicians should be aware, however, that oligohydramnios may not appear until after the fetus has sustained irreversible injury. Closely observe infants with histories of in utero exposure to Lotensin for hypotension, oliguria, and hyperkalemia. If oliguria or hypotension occur in neonates with a history of in uteroexposure to Lotensin, support blood pressure and renal perfusion. Exchange transfusions or dialysis may be required as a means of reversing hypotension and substituting for disordered renal function.

8.2 Lactation

Minimal amounts of unchanged benazepril and of benazeprilat are excreted into the breast milk of lactating women treated with benazepril. A newborn child ingesting entirely breast milk would receive less than 0.1% of the mg/kg maternal dose of benazepril and benazeprilat.

8.3 Pediatric Use

The antihypertensive effects of Lotensin have been evaluated in a double-blind study in pediatric patients 7 to 16 years of age [see Clinical Pharmacology (12.3)]. The pharmacokinetics of Lotensin have been evaluated in pediatric patients 6 to 16 years of age [see Clinical Pharmacology (12.3)].

Infants below the age of 1 year should not be given Lotensin because of the risk of effects on kidney development.

Safety and effectiveness of Lotensin have not been established in pediatric patients less than 6 years of age or in children with glomerular filtration rate < 30 mL/min/1.73m² [see Dosage and Administration (2.1) and Clinical Pharmacology 12.3)].

8.4 Geriatric Use

Of the total number of patients who received benazepril in U.S. clinical studies of Lotensin, 18% were 65 or older while 2% were 75 or older. No overall differences in effectiveness or safety were observed between these patients and younger patients, and other reported clinical experience has not identified differences in responses between the elderly and younger patients, but greater sensitivity of some older individuals cannot be ruled out.

Benazepril and benazeprilat are substantially excreted by the kidney. Because elderly patients are more likely to have decreased renal function, care should be taken in dose selection, and it may be useful to monitor renal function [see Dosage and Administration (2.2)].

8.5 Race

ACE inhibitors, including Lotensin, as monotherapy, have an effect on blood pressure that is less in Black patients than in non-Blacks.

8.6 Renal Impairment

Dose adjustment of Lotensin is required in patients undergoing hemodialysis or whose creatinine clearance is ≤ 30 mL/min. No dose adjustment of Lotensin is required in patients with creatinine clearance > 30 mL/min [see Dosage and Administration (2.2) and Clinical Pharmacology (12.3)].

10. OVERDOSAGE

Single oral doses of 3 g/kg benazepril were associated with significant lethality in mice. Rats, however, tolerated single oral doses of up to 6 g/kg. Reduced activity was seen at

1 g/kg in mice and at 5 g/kg in rats. Human overdoses of benazepril have not been reported, but the most common manifestation of human benazepril overdosage is likely to be hypotension, for which the usual treatment would be intravenous infusion of normal saline solution. Hypotension can be associated with electrolyte disturbances and renal failure.

Benazepril is only slightly dialyzable, but consider dialysis to support patients with severely impaired renal function [see Warnings and Precautions (5.3)].

If ingestion is recent, consider activated charcoal. Consider gastric decontamination (e.g., vomiting, gastric lavage) in the early period after ingestion.

Monitor for blood pressure and clinical symptoms. Supportive management should be employed to ensure adequate hydration and to maintain systemic blood pressure.

In the case of marked hypotension, infuse physiological saline solution; as needed, consider vasopressors (e.g., catecholamines i.v.).

11. DESCRIPTION

Benazepril hydrochloride, USP is a white to off-white crystalline powder, soluble (> 100 mg/mL) in water, in ethanol, and in methanol. Its chemical name is benazepril 3-[[1-(ethoxy-carbonyl)-3 phenyl-(1S)-propyl]amino]-2,3,4,5-tetrahydro-2-oxo-1 H-1-(3S)-benzazepine-1-acetic acid monohydrochloride; its structural formula is

Its empirical formula is C24H28N2O5•HCl, and its molecular weight is 460.96.

Benazeprilat, the active metabolite of benazepril, is a non-sulfhydryl angiotensin-converting enzyme inhibitor.

Lotensin is supplied as tablets containing 10 mg, 20 mg, and 40 mg of benazepril hydrochloride for oral administration. The inactive ingredients are colloidal silicon dioxide, crospovidone, hydrogenated castor oil (10 mg and 20 mg tablets), hypromellose, iron oxides, lactose, magnesium stearate (40 mg tablets), microcrystalline cellulose, polysorbate 80, propylene glycol (40 mg tablets), starch, talc, and titanium dioxide.

12. CLINICAL PHARMACOLOGY

12.1 Mechanism of Action

Benazepril and benazeprilat inhibit angiotensin-converting enzyme (ACE) in human subjects and animals. Benazeprilat has much greater ACE inhibitory activity than does benazepril.

ACE is a peptidyl dipeptidase that catalyzes the conversion of angiotensin I to the vasoconstrictor substance, angiotensin II. Angiotensin II also stimulates aldosterone secretion by the adrenal cortex.

Inhibition of ACE results in decreased plasma angiotensin II, which leads to decreased vasopressor activity and to decreased aldosterone secretion. The latter decrease may result in a small increase of serum potassium.

Removal of angiotensin II negative feedback on renin secretion leads to increased plasma renin activity. In animal studies, benazepril had no inhibitory effect on the vasopressor response to angiotensin II and did not interfere with the hemodynamic effects of the autonomic neurotransmitters acetylcholine, epinephrine, and norepinephrine.

ACE is identical to kininase, an enzyme that degrades bradykinin. Whether increased levels of bradykinin, a potent vasodepressor peptide, play a role in the therapeutic effects of Lotensin remains to be elucidated. While the mechanism through which benazepril lowers blood pressure is believed to be primarily suppression of the renin-angiotensin-aldosterone system, benazepril has an antihypertensive effect even in patients with low-renin hypertension.

12.2 Pharmacodynamics

Single and multiple doses of 10 mg or more of Lotensin cause inhibition of plasma ACE activity by at least 80% to 90% for at least 24 hours after dosing. Pressor responses to exogenous angiotensin I were inhibited by 60% to 90% (up to 4 hours post-dose) at the 10 mg dose.

Drug Interactions

Lotensin has been used concomitantly with beta-adrenergic-blocking agents, calcium- channel-blocking agents, diuretics, digoxin, and hydralazine, without evidence of clinically important adverse interactions. Benazepril, like other ACE inhibitors, has had less than additive effects with beta-adrenergic blockers, presumably because both drugs lower blood pressure by inhibiting parts of the renin-angiotensin system.

12.3 Pharmacokinetics

The pharmacokinetics of benazepril are approximately dose-proportional within the dosage range of 10 to 80 mg.

Following oral administration of Lotensin, peak plasma concentrations of benazepril, and its active metabolite benazeprilat are reached within 0.5 to1.0 hour and 1 to 2 hours, respectively. While the bioavailability of benazepril is not affected by food, time to peak plasma concentrations of benazeprilat is delayed to 2 to 4 hours.

The serum protein binding of benazepril is about 96.7% and that of benazeprilat about 95.3%, as measured by equilibrium dialysis; on the basis of in vitrostudies, the degree of protein binding should be unaffected by age, hepatic dysfunction, or concentration (over the concentration range of 0.24 - 23.6 µmol/L).

Benazepril is almost completely metabolized to benazeprilat by cleavage of the ester group (primarily in liver). Both benazepril and benazeprilat undergo glucuronidation.

Benazepril and benazeprilat are cleared predominantly by renal excretion. About 37% of an orally administered dose was recovered in urine as benazeprilat (20%), benazeprilat glucuronide (8%), benazepril glucuronide (4%) and as trace amounts of benazepril. Nonrenal (i.e., biliary) excretion accounts for approximately 11% to 12% of benazeprilat excretion. The effective half-life of benazeprilat following once daily repeat oral administration of benazepril hydrochloride is 10 to 11 hours. Thus, steady-state concentrations of benazeprilat should be reached after 2 or 3 doses of benazepril hydrochloride given once daily.

Accumulation ratio based on AUC of benazeprilat was 1.19 following once daily administration.

Specific Populations

Renalimpairment

The pharmacokinetics of systemic exposure to benazepril and benazeprilat in patients with mild-to-moderate renal insufficiency (creatinine clearance > 30 mL/min) is similar to that in patients with normal renal function. In patients with creatinine clearance ≤ 30 mL/min, peak benazeprilat levels and the initial (alpha phase) half-life increase, and time to steady-state may be delayed [see Dosage and Administration (2)].

When dialysis was started 2 hours after ingestion of 10 mg of benazepril, approximately 6% of benazeprilat was removed in 4 hours of dialysis. The parent compound, benazepril, was not detected in the dialysate.

Hepaticimpairment

In patients with hepatic insufficiency (due to cirrhosis) ,the pharmacokinetics of benazeprilat are essentially unaltered.

Drug Interactions

The pharmacokinetics of benazepril are not affected by the following drugs: hydrochlorothiazide, furosemide, chlorthalidone, digoxin, propranolol, atenolol, nifedipine, amlodipine, naproxen, acetylsalicylic acid, or cimetidine. Likewise the administration of benazepril does not substantially affect the pharmacokinetics of these medications (cimetidine kinetics were not studied).

Pediatrics

The pharmacokinetics of benazaprilat, evaluated in pediatric patients with hypertension following oral administration of a single dose is presented in table below.

Agegroup | Cmax (ng/mL) | Tmax* (h) | AUC 0-inf (ng/mL*h) | CL/F/wt (L/h/Kg) | T 1/2 (h)
>1 to ≤ 24 months | 277 | 1 | 1328 | 0.26 | 5.0
n=5 | (192, 391) | (0.6, 2) | (773, 2117) | (0.18, 0.4) | (4, 5.8)
>2 to ≤ 6 years | 200 | 2 | 978 | 0.36 | 5.5
n=7 | (168, 244) | (1.4, 2.4) | (842, 1152) | (0.31, 0.42) | (4.7, 6.5)
>6 to ≤ 12 years | 221 | 2 | 1041 | 0.25 | 5.5
n=7 | (194, 258) | (1.2, 2.2) | (855, 1313) | (0.21, 0.31) | (4.7, 6.5)
>12 to ≤ 17 years | 287 | 2 | 1794 | 0.16 | 5.1
n=8 | (217, 420) | (1.3, 2.3) | (1478, 2340) | (0.13, 0.21) | (4.2, 5.7)

13. NONCLINICAL TOXICOLOGY

13.1 Carcinogenesis, Mutagenesis, Impairment of Fertility

No evidence of carcinogenicity was found when benazepril was administered to rats and mice for up to two years at doses of up to 150 mg/kg/day. When compared on the basis of body weights, this dose is 110 times the maximum recommended human dose. When compared on the basis of body surface areas, this dose is 18 and 9 times (rats and mice, respectively) the maximum recommended human dose (calculations assume a patient weight of 60 kg). No mutagenic activity was detected in the Ames test in bacteria (with or without metabolic activation), in an in vitrotest for forward mutations in cultured mammalian cells, or in a nucleus anomaly test. In doses of 50 to 500 mg/kg/day (6 to 60 times the maximum recommended human dose based on mg/m²comparison and 37 to 375 times the maximum recommended human dose based on a mg/kg comparison), Lotensin had no adverse effect on the reproductive performance of male and female rats.

14. CLINICAL STUDIES

Hypertension

Adult Patients

In single-dose studies, Lotensin lowered blood pressure within 1 hour, with peak reductions achieved between 2 and 4 hours after dosing. The antihypertensive effect of a single dose persisted for 24 hours. In multiple-dose studies, once-daily doses of between 20 mg and 80 mg decreased seated pressure 24 hours after dosing by about 6 to 12 mm Hg systolic and 4 to 7 mm Hg diastolic. The trough values represent reductions of about 50% of that seen at peak.

Four dose-response studies using once-daily dosing were conducted in 470 mild-to-moderate hypertensive patients not using diuretics. The minimal effective once-daily dose of Lotensin was 10 mg; but further falls in blood pressure, especially at morning trough, were seen with higher doses in the studied dosing range (10 to 80 mg). In studies comparing the same daily dose of Lotensin given as a single morning dose or as a twice-daily dose, blood pressure reductions at the time of morning trough blood levels were greater with the divided regimen.

The antihypertensive effects of Lotensin were not appreciably different in patients receiving high- or low-sodium diets.

In normal human volunteers, single doses of benazepril caused an increase in renal blood flow but had no effect on glomerular filtration rate.

Use of Lotensin in combination with thiazide diuretics gives a blood-pressure-lowering effect greater than that seen with either agent alone. By blocking the renin-angiotensin-aldosterone axis, administration of Lotensin tends to reduce the potassium loss associated with the diuretic.

Pediatric Patients

In a clinical study of 107 pediatric patients, 7 to 16 years of age, with either systolic or diastolic pressure above the 95th percentile, patients were given 0.1 or 0.2 mg/kg then titrated up to 0.3 or 0.6 mg/kg with a maximum dose of 40 mg once daily. After four weeks of treatment, the 85 patients whose blood pressure was reduced on therapy were then randomized to either placebo or benazepril and were followed up for an additional two weeks. At the end of two weeks, blood pressure (both systolic and diastolic) in children withdrawn to placebo rose by 4 to 6 mm Hg more than in children on benazepril. No dose-response was observed.

16. HOW SUPPLIED/STORAGE AND HANDLING

Lotensin is available as:

Dose | Color | Engraving | Bottle of 100
10 mg | Dark Yellow | Lotensin 10 | NDC 30698-448-01
20 mg | Pink | Lotensin 20 | NDC 30698-449-01
40 mg | Dark Rose | Lotensin 40 | NDC 30698-450-01

Storage: Do not store above 86°F (30ºC). Protect from moisture. Dispense in a tight container (USP).

17. PATIENT COUNSELING INFORMATION

Pregnancy: Tell female patients of childbearing age about the consequences of exposure to Lotensin during pregnancy. Discuss treatment options with women planning to become pregnant. Instruct patients to report pregnancies to their physicians as soon as possible.

Angioedema: Angioedema, including laryngeal edema, can occur at any time with treatment with ACE inhibitors. Tell patients to report immediately any signs or symptoms suggesting angioedema (swelling of face, eyes, lips, or tongue, or difficulty in breathing) and to take no more drugs until they have consulted with the prescribing physician.

Symptomatic Hypotension: Tell patients to report light-headedness especially during the first few days of therapy. If actual syncope occurs, tell the patients to discontinue the drug until they have consulted with the prescribing physician.

Tell patients that excessive perspiration and dehydration may lead to an excessive fall in blood pressure because of a reduction in fluid volume. Other causes of volume depletion such as vomiting or diarrhea may also lead to a fall in blood pressure; advise patients accordingly.

Hyperkalemia: Tell patients not to use potassium supplements or salt substitutes containing potassium without consulting the prescribing physician.

Hypoglycemia: Tell diabetic patients treated with oral antidiabetic agents or insulin starting an ACE inhibitor to monitor for hypoglycemia closely, especially during the first month of combined use.

Manufactured for and Distributed by:
Validus Pharmaceuticals LLC
Parsippany, NJ 07054
info@validuspharma.com
www.validuspharma.com
1-866-982-5438 (1-866-9VALIDUS)

Product of China

© 2018 Validus Pharmaceuticals LLC

60023-05 January 2019

PACKAGE LABEL

PRINCIPAL DISPLAY PANEL

NDC 30698-448-01
Lotensin
(benazepril HCI USP)
10 mg
100 Tablets
Rx Only

PACKAGE LABEL

PRINCIPAL DISPLAY PANEL

NDC 30698-449-01
Lotensin
(benazepril HCI USP)
20 mg
100 Tablets
Rx Only

PACKAGE LABEL

PRINCIPAL DISPLAY PANEL

NDC 30698-450-01
Lotensin
(benazepril HCI USP)
40 mg
100 Tablets
Rx Only